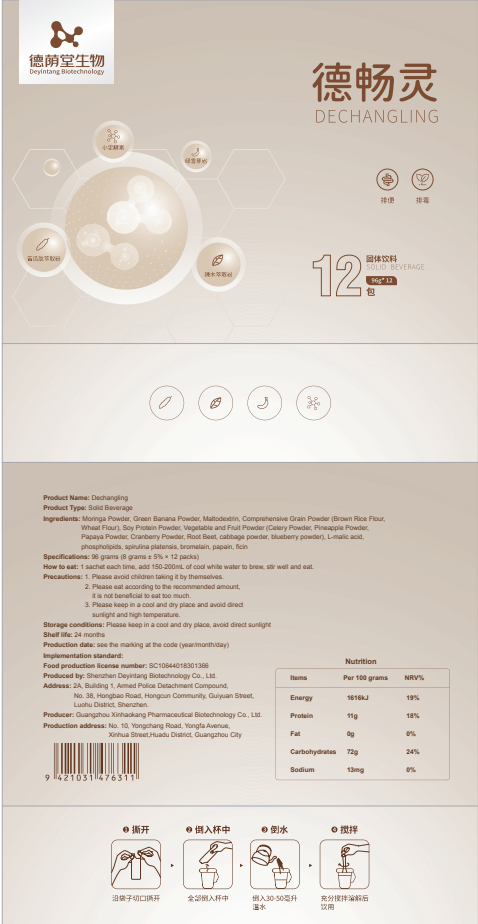 DRUG LABEL: Dechangling
NDC: 82570-009 | Form: POWDER
Manufacturer: Shenzhen Deyintang Biotechnology Co., Ltd.
Category: otc | Type: HUMAN OTC DRUG LABEL
Date: 20220221

ACTIVE INGREDIENTS: BANANA 10 g/100 g; MORINGA OLEIFERA LEAF 10 g/100 g; MOMORDICA CHARANTIA WHOLE 10 g/100 g; PSYLLIUM HUSK 2 g/100 g; APPLE CIDER 2 g/100 g; ASPERGILLOPEPSIN I (ASPERGILLUS PHOENICIS) 2 g/100 g; AMYLOGLUCOSIDASE (ASPERGILLUS NIGER) 2 g/100 g; PANCRELIPASE LIPASE 2 g/100 g; PAPAIN 2 g/100 g; KIWI FRUIT 2 g/100 g; .ALPHA.-TOCOPHEROL 2 g/100 g; SENNA OBTUSIFOLIA SEED 2 g/100 g
INACTIVE INGREDIENTS: MALTODEXTRIN; CITRIC ACID MONOHYDRATE; SUCRALOSE; ANHYDROUS DEXTROSE; MALUS DOMESTICA POLLEN

ACTIVE INGREDIENT

Moringa Powder,Green Banana Powder,Maltodextrin, Comprehensive Grain Powder (Brown Rice Flour,Wheat Flour), Soy Protein Powder,Vegetable and Fruit Powder(Celery Powder, Pineapple Powder,Papaya Powder, Cranberry Powder, Root Beet, cabbage powder, blueberry powder),

INACTIVE INGREDIENT

L-malic acid,phospholipids,spirulina platensis, bromelain, papain, ficin

PURPOSE

health care

Please avoid children taking it by themselves.

How to eat

1 sachet each time, add 150-200mL of cool white water to brew, stir well and eat.

INDICATIONS AND USAGE

Please eat according to the recommended amount,it is not beneficial to eat too much.

Storage conditions

Please keep in a cool and dry place, avoid direct sunlight

WARNINGS

1. Please avoid children taking it by themselves.
2.Please eat according to the recommended amount,it is not beneficial to eat too much.
3. Please keep in a cool and dry place and avoid directsunlight and high temperature.